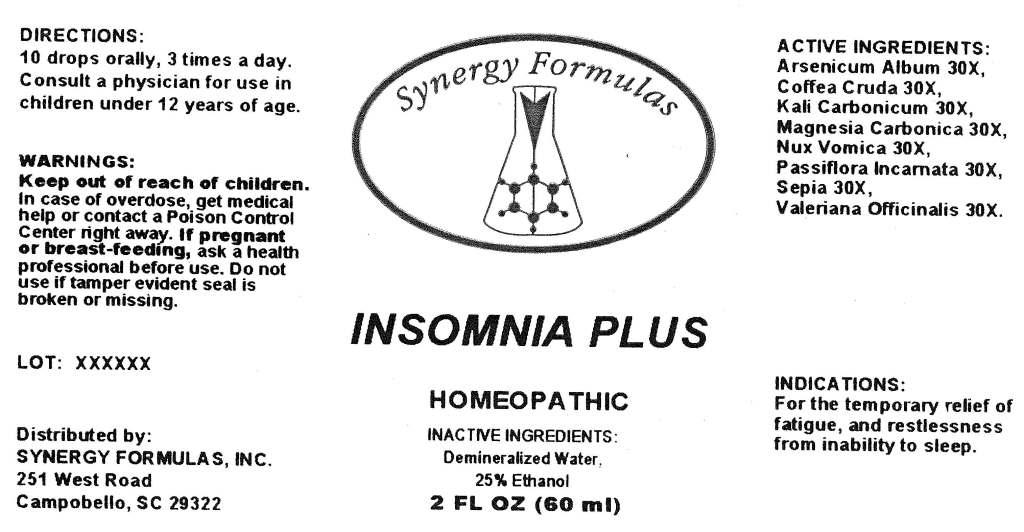 DRUG LABEL: Insomnia Plus
NDC: 57520-0611 | Form: LIQUID
Manufacturer: Apotheca Company
Category: homeopathic | Type: HUMAN OTC DRUG LABEL
Date: 20110610

ACTIVE INGREDIENTS: ARSENIC TRIOXIDE 30 [hp_X]/1 mL; ARABICA COFFEE BEAN 30 [hp_X]/1 mL; POTASSIUM CARBONATE 30 [hp_X]/1 mL; MAGNESIUM CARBONATE 30 [hp_X]/1 mL; STRYCHNOS NUX-VOMICA SEED 30 [hp_X]/1 mL; PASSIFLORA INCARNATA TOP 30 [hp_X]/1 mL; SEPIA OFFICINALIS JUICE 30 [hp_X]/1 mL; VALERIAN 30 [hp_X]/1 mL
INACTIVE INGREDIENTS: WATER; ALCOHOL

Insomnia Plus

ACTIVE INGREDIENT

ACTIVE INGREDIENTS: Arsenicum album 30X, Coffea cruda 30X, Kali carbonicum 30X, Magnesia carbonica 30X, Nux vomica 30X, Passiflora incarnata 30X, Sepia 30X, Valeriana officinalis 30X.

PURPOSE

INDICATIONS: For the temporary relief of fatigue, and restlessness from inability to sleep.

WARNINGS

WARNINGS: Keep out of reach of children. In case of overdose, get medical help or contact a Poison Control Center right away.

If pregnant or breast-feeding, ask a health professional before use.

Do not use if tamper evident seal is broken or missing.

DOSAGE AND ADMINISTRATION

DIRECTIONS: 10 drops orally, 3 times a day. Consult a physician for use in children under 12 years of age.

INACTIVE INGREDIENTS: Demineralized water, 25% Ethanol.

KEEP OUT OF REACH OF CHILDREN. In case of overdose, get medical help or contact a Poison Control Center right away.

INDICATIONS AND USAGE

INDICATIONS: For the temporary relief of fatigue, and restlessness from inability to sleep.

QUESTIONS

Distributed by:

SYNERGY FORMULAS, INC.

251 West Road

Campobello, SC 29322

PACKAGE LABEL

Synergy Formulas

INSOMNIA PLUS

HOMEOPATHIC

2 FL OZ (60 ml)